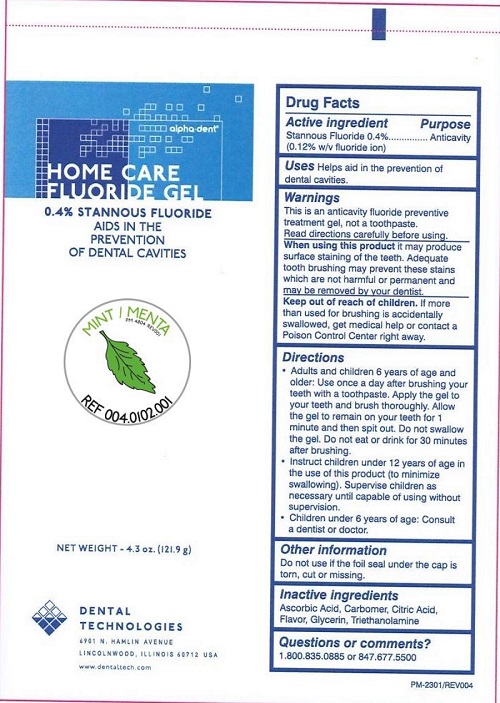 DRUG LABEL: Home Care Fluoride
NDC: 55346-0401 | Form: GEL
Manufacturer: Dental Technologies, Inc.
Category: otc | Type: HUMAN OTC DRUG LABEL
Date: 20251104

ACTIVE INGREDIENTS: STANNOUS FLUORIDE 0.969 mg/1 g
INACTIVE INGREDIENTS: ASCORBIC ACID; ANHYDROUS CITRIC ACID; GLYCERIN; TROLAMINE; CARBOMER HOMOPOLYMER TYPE B (ALLYL SUCROSE CROSSLINKED)

DTI Stannous - Mint

Active ingredient

Stannous Fluoride 0.4%

(0.12% w/v flurodie ion)

Purpose

Anticavity

Uses

Helps aid in the prevention of dental cavities.

Warnings

This is an anticavity fluoride preventive treatment gel, not a toothpaste.

Read directions carefully before using.

When using this product

it may produce surface staining of the teeth. Adequate tooth brushing may prevent these stains which are not harmful to permanent and may be removed by your dentist.

Keep out of reach of children.

If more than used for brushing is accidentally swallowed, get medical help or contact a Poison Control Center right away.

Directions

- Adults and children 6 years of age and older: Use once a day after brushing your teeth with a toothpaste. Apply the gel to your teeth and brush thoroughly. Allow the gel to remain on your teeth for 1 minute and then spit out. Do not swallow the gel. Do not eat or drink for 30 minutes after brushing.
- Instruct children under 12 years of age in the use of this product (to minimize swallowing). Supervise children as necessary until capable of using without supervision.
- Children under 6 years of age: Consult a dentist or doctor.

Other information

Do not use if the foil seal under the cap is torn, cut or missing.

Inactive ingredients

Ascorbic Acid, Carbomer, Citric Acid, Flavor, Glycerin, Triethanolamine

Questions or comments?

1.800.835.0885 or 847.677.5500

Principal Display Panel

alpha-dent®

HOME CARE

FLUORIDE GEL

0.4% STANNOUS FLUORIDE

AIDS IN THE

PREVENTION

OF DENTAL CAVITIES

MINT

REF 004.0102.001

NET WEIGHT - 4.3 oz. (121.9g)

DENTAL

TECHNOLOGIES

6901 N HAMLIN AVENUE

LINCOLNWOOD, ILLINOIS 60712 USA

www.dentaltech.com